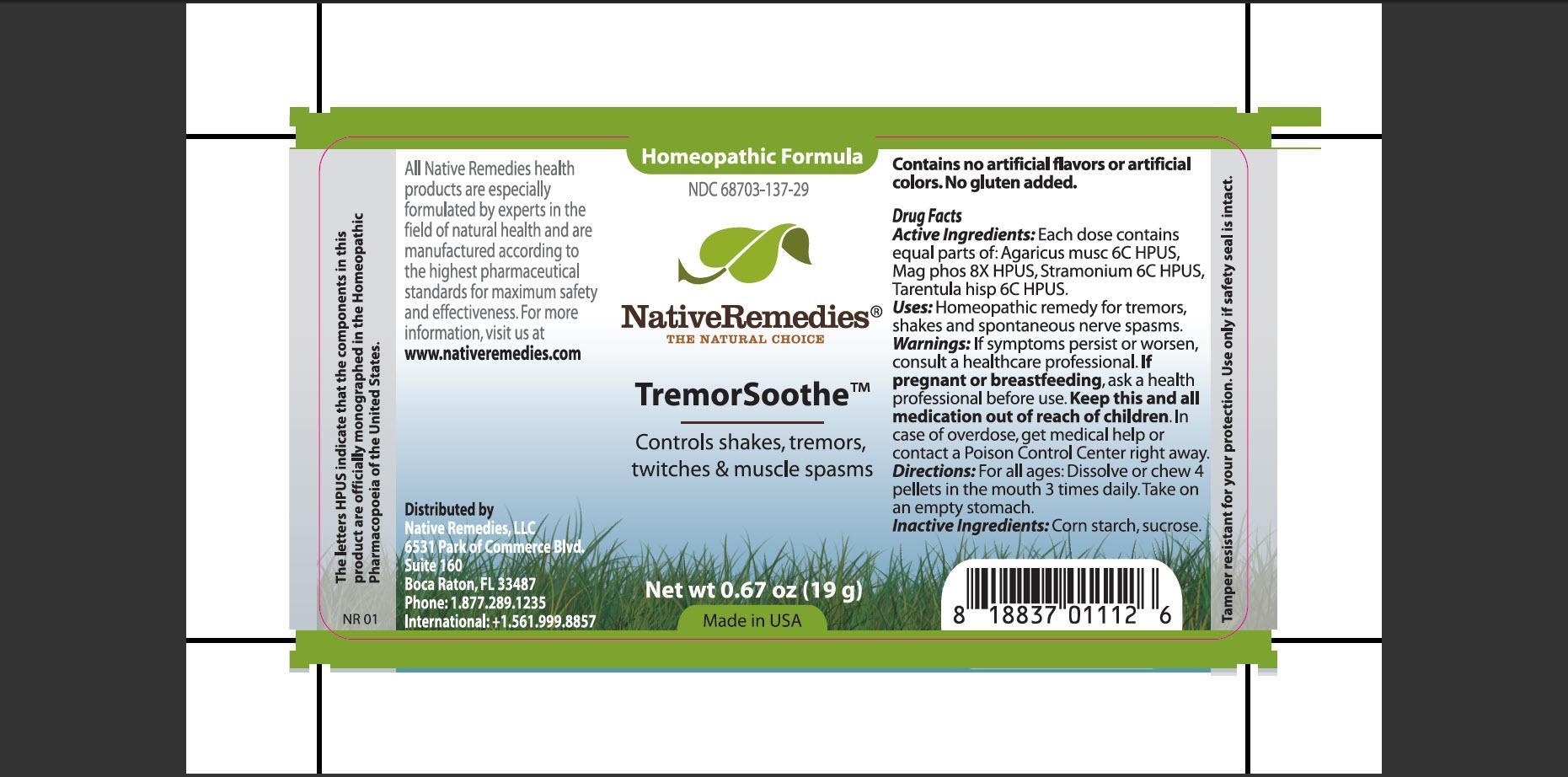 DRUG LABEL: TremorSoothe
NDC: 68703-137 | Form: PELLET
Manufacturer: Native Remedies, LLC
Category: homeopathic | Type: HUMAN OTC DRUG LABEL
Date: 20130828

ACTIVE INGREDIENTS: AMANITA MUSCARIA FRUITING BODY 6 [hp_C]/19 g; MAGNESIUM PHOSPHATE, DIBASIC TRIHYDRATE 8 [hp_X]/19 g; DATURA STRAMONIUM 6 [hp_C]/19 g; LYCOSA TARANTULA 6 [hp_C]/19 g
INACTIVE INGREDIENTS: STARCH, CORN; SUCROSE

TremorSoothe

PURPOSE

Controls shakes, tremors, twitches and muscle spasms

Drug Facts
Active Ingredients:Each dose contains equal parts of: Agaricus musc 6C HPUS, Mag phos 8X HPUS, Stramonium 6C HPUS, Tarentula hisp 6C HPUS

INDICATIONS AND USAGE

Uses:Homeopathic remedy for tremors, shakes and spontaneous nerve spasms

WARNINGS

Warnings: If symptoms persist or worsen, consult a healthcare professional

PREGNANCY OR BREAST FEEDING

If pregnant or breastfeeding, ask a health professional before use

KEEP OUT OF REACH OF CHILDREN

Keep this and all medication out of reach of children

OVERDOSAGE

In case of overdose, get medical help or contact a Poison Control Center right away

DOSAGE AND ADMINISTRATION

Directions:For all ages: Dissolve or chew 4 pellets in the mouth 3 times daily. Take on empty stomach

Inactive Ingredients: Corn starch, sucrose

PATIENT COUNSELING INFORMATION

The letters HPUS indicate that the components in this product are officially monographed in the Homeopathic Pharmacopoeia of the United States

All Native Remedies health products are especially formulated by experts in the field of natural health and are manufactured according to the highest pharmaceutical standards for maximum safety and effectiveness. For more information, visit us at www.nativeremedies.com

Distributed by
Native Remedies, LLC
6531 Park of Commerce Blvd.
Suite 160
Boca Raton, FL 33487
Phone: 1.877.289.1235
International: +1.561.999.8857

Contains no artificial flavors or artificial colors. No gluten added

STORAGE AND HANDLING

Tamper resistant for your protection. Use only if safety seal is intact